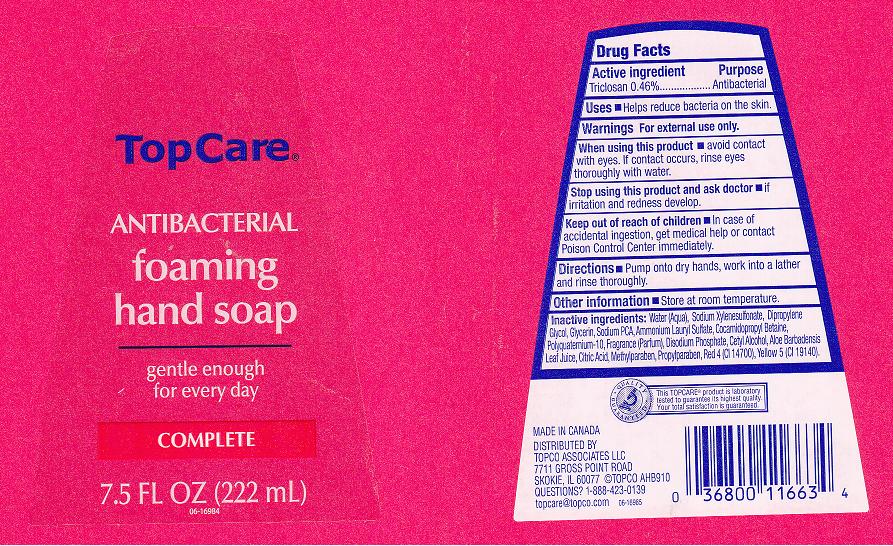 DRUG LABEL: ANTIBACTERIAL FOAMING 
NDC: 36800-177 | Form: LIQUID
Manufacturer: TOPCO ASSOCIATES LLC
Category: otc | Type: HUMAN OTC DRUG LABEL
Date: 20111107

ACTIVE INGREDIENTS: TRICLOSAN 0.46 mL/100 mL
INACTIVE INGREDIENTS: WATER; SODIUM  XYLENESULFONATE; DIPROPYLENE GLYCOL; GLYCERIN; SODIUM PYRROLIDONE CARBOXYLATE; AMMONIUM LAURYL SULFATE; COCAMIDOPROPYL BETAINE; POLYQUATERNIUM-10 (400 CPS AT 2%); SODIUM PHOSPHATE, DIBASIC, DIHYDRATE; CETYL ALCOHOL; ALOE VERA LEAF; CITRIC ACID MONOHYDRATE; METHYLPARABEN; PROPYLPARABEN; FD&C RED NO. 4; FD&C YELLOW NO. 5

DRUG FACTS

Active Ingredient

Triclosan 0.46%

Purpose

Antibacterial

Uses

Helps reduce bacteria on the skin.

Warnings

For external use only.

When using this product

Avoid contact with eyes. If contact occurs, rinse eyes thoroughly with water.

Stop using this product and ask doctor if

Irritation and redness develop.

Keep out of reach of children

In case of accidental ingestion, get medical help and contact Poison Control Center immediately.

Directions

Pump onto dry hands, work into a lather and rinse thoroughly.

Other information

Store at room temperature.

Inactive Ingredients

WATER, SODIUM XYLENESULFONATE, DIPROPYLENE GLYCOL, GLYCERIN, SODIUM PCA, AMMONIUM LAURYL SULFATE, COCAMIDOPROPYL BETAINE, POLYQUATERNIUM-10, FRAGRANCE, DISODIUM PHOSPHATE, CETYL ALCOHOL, ALOE BARBADENSIS LEAF JUICE, CITRIC ACID, METHYLPARABEN, PROPYLPARABEN, RED 4 (CI 14700), YELLOW 5 (CI 19140).